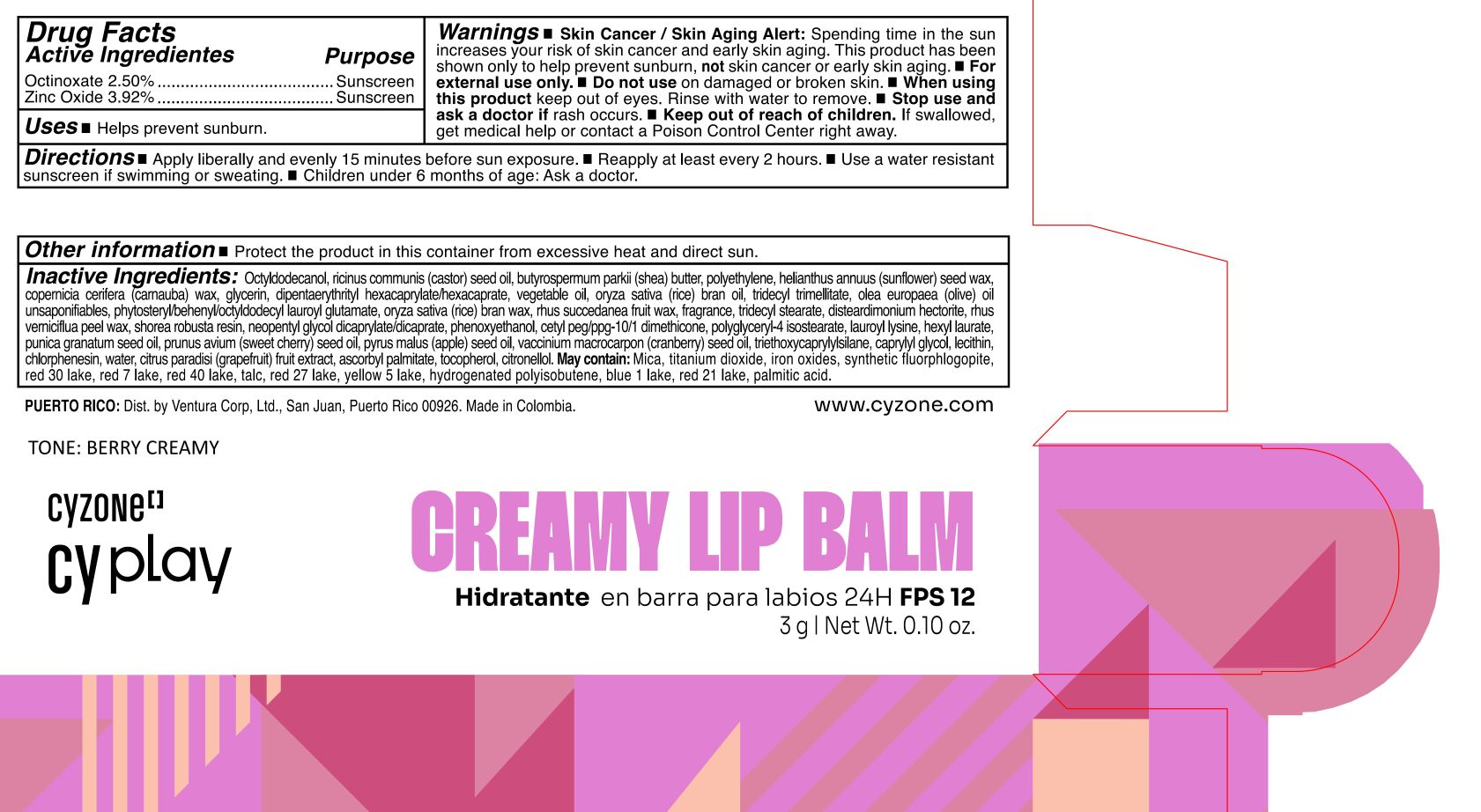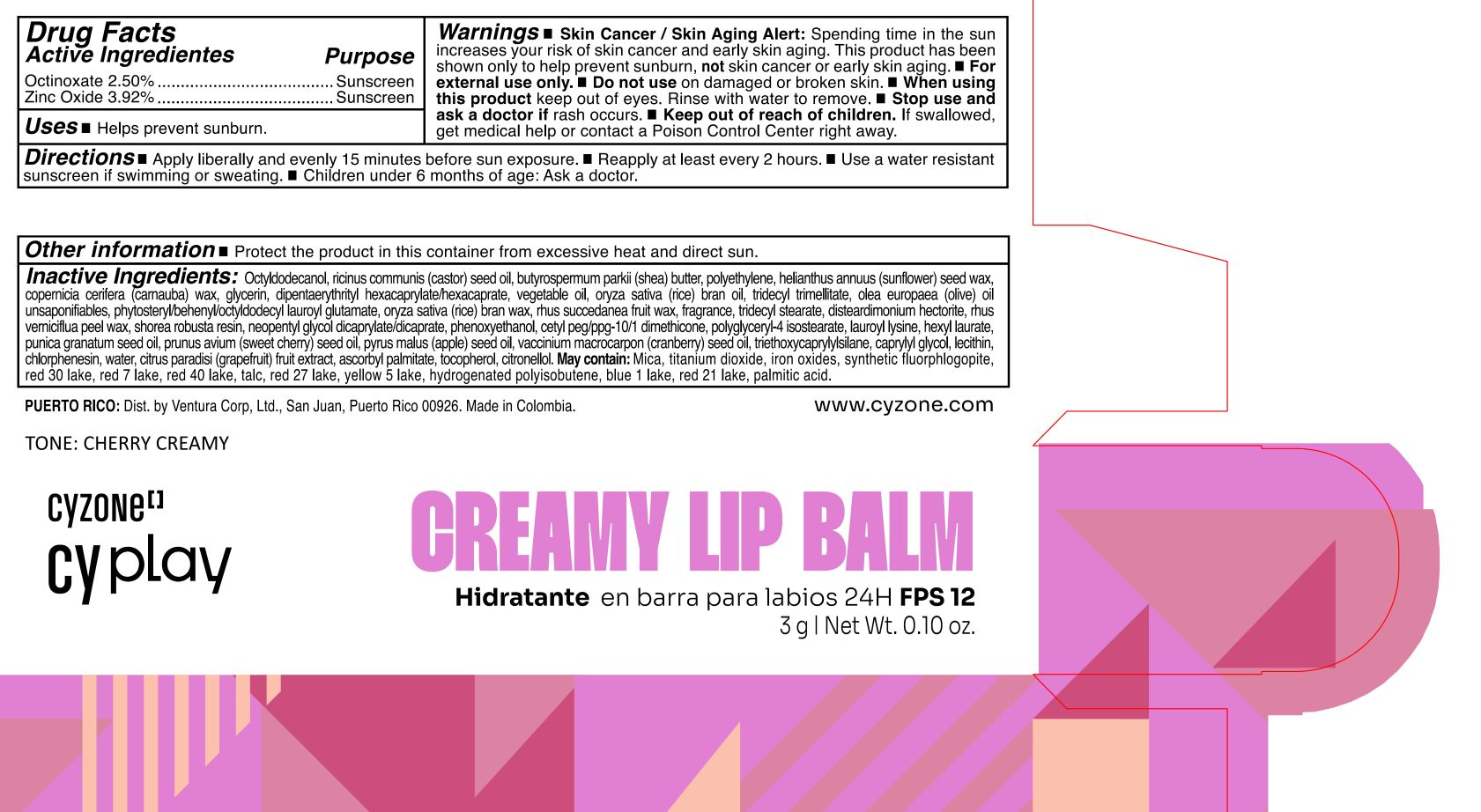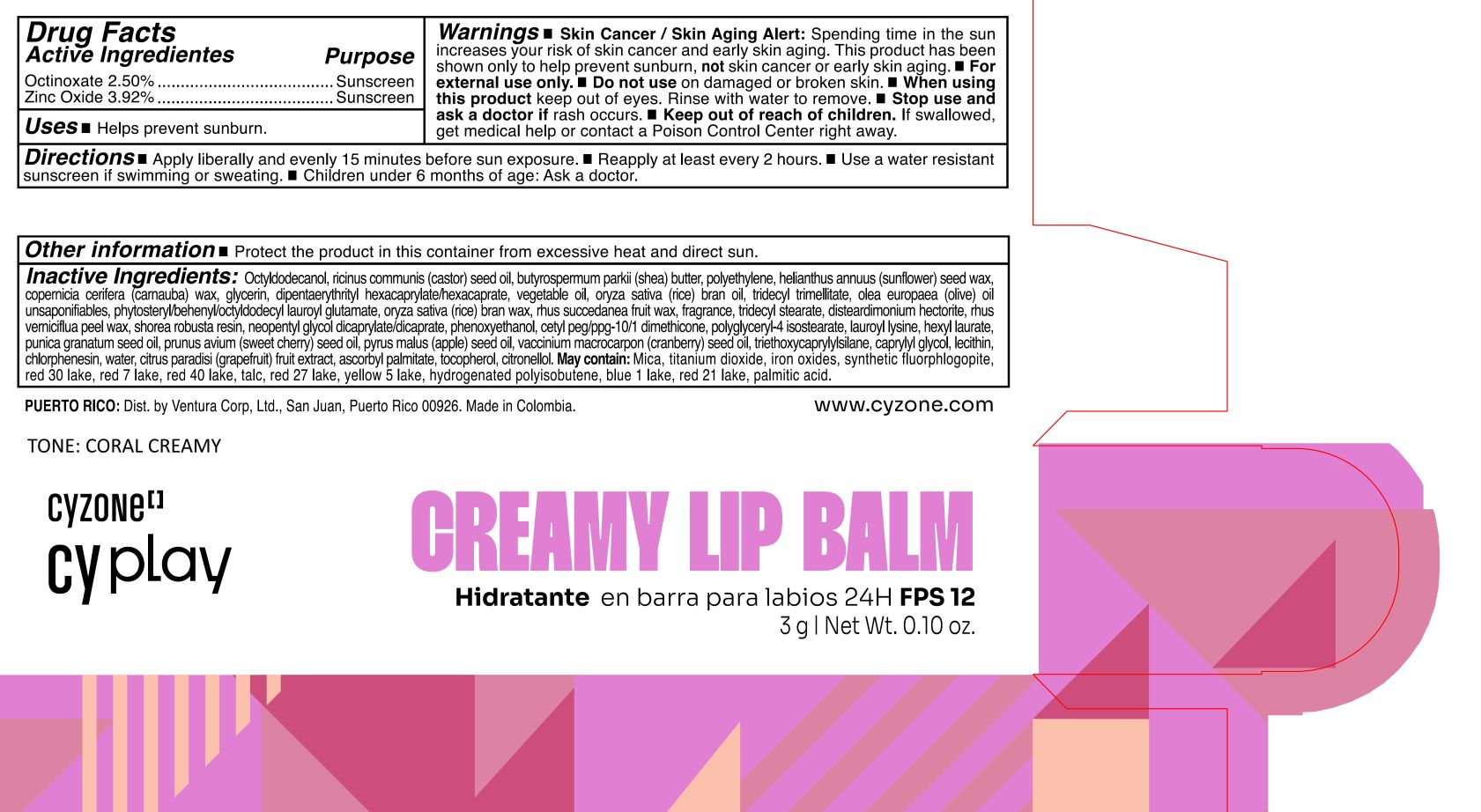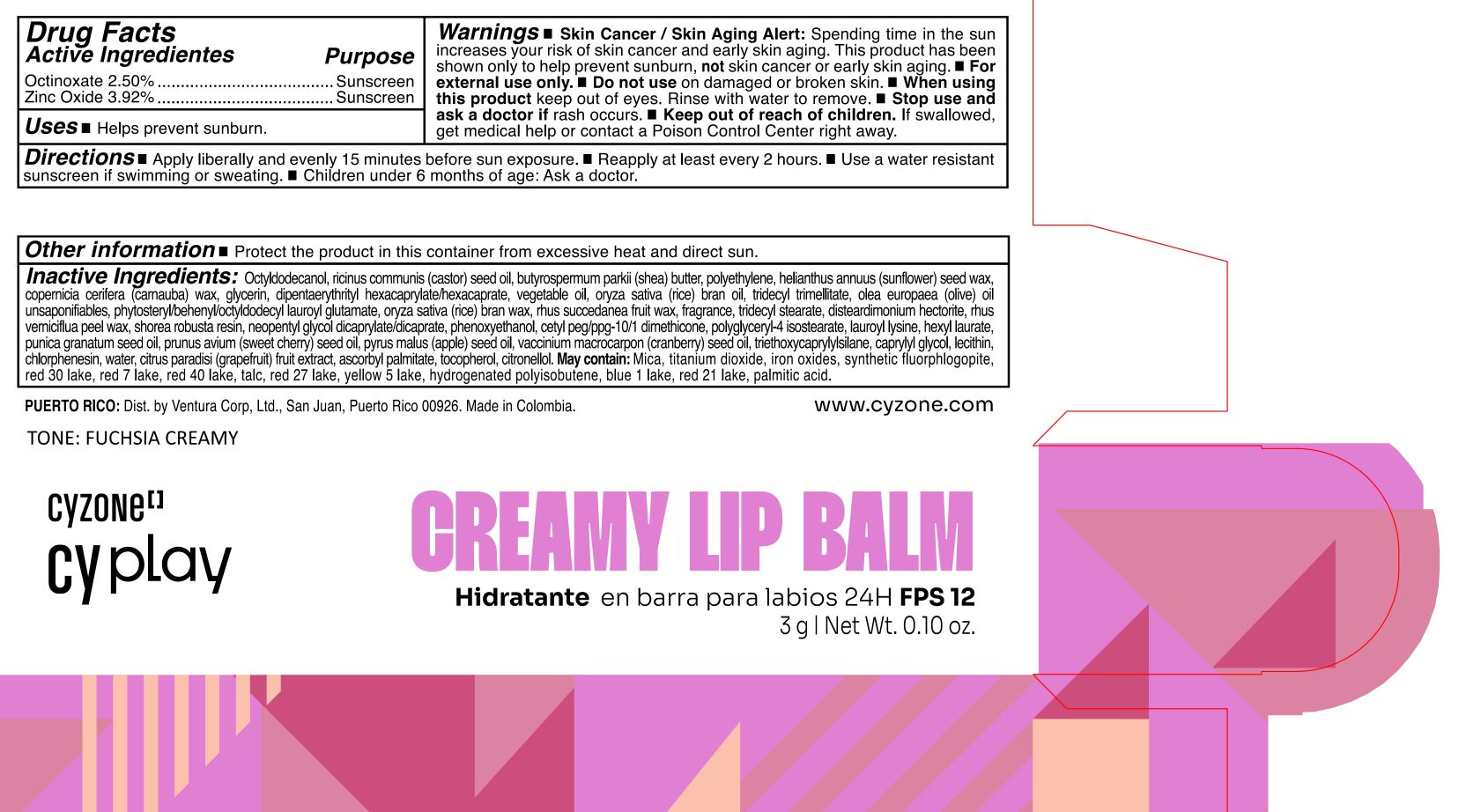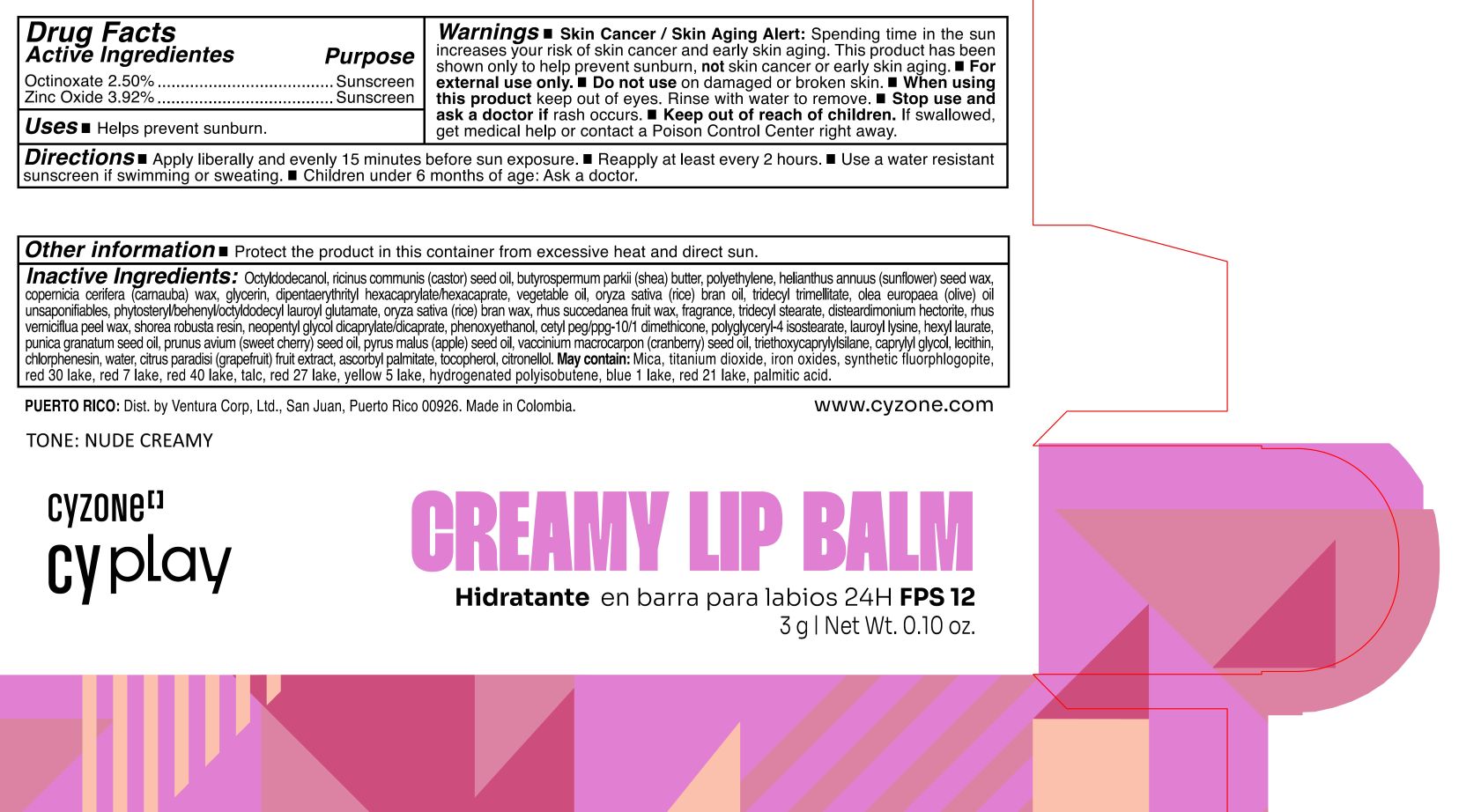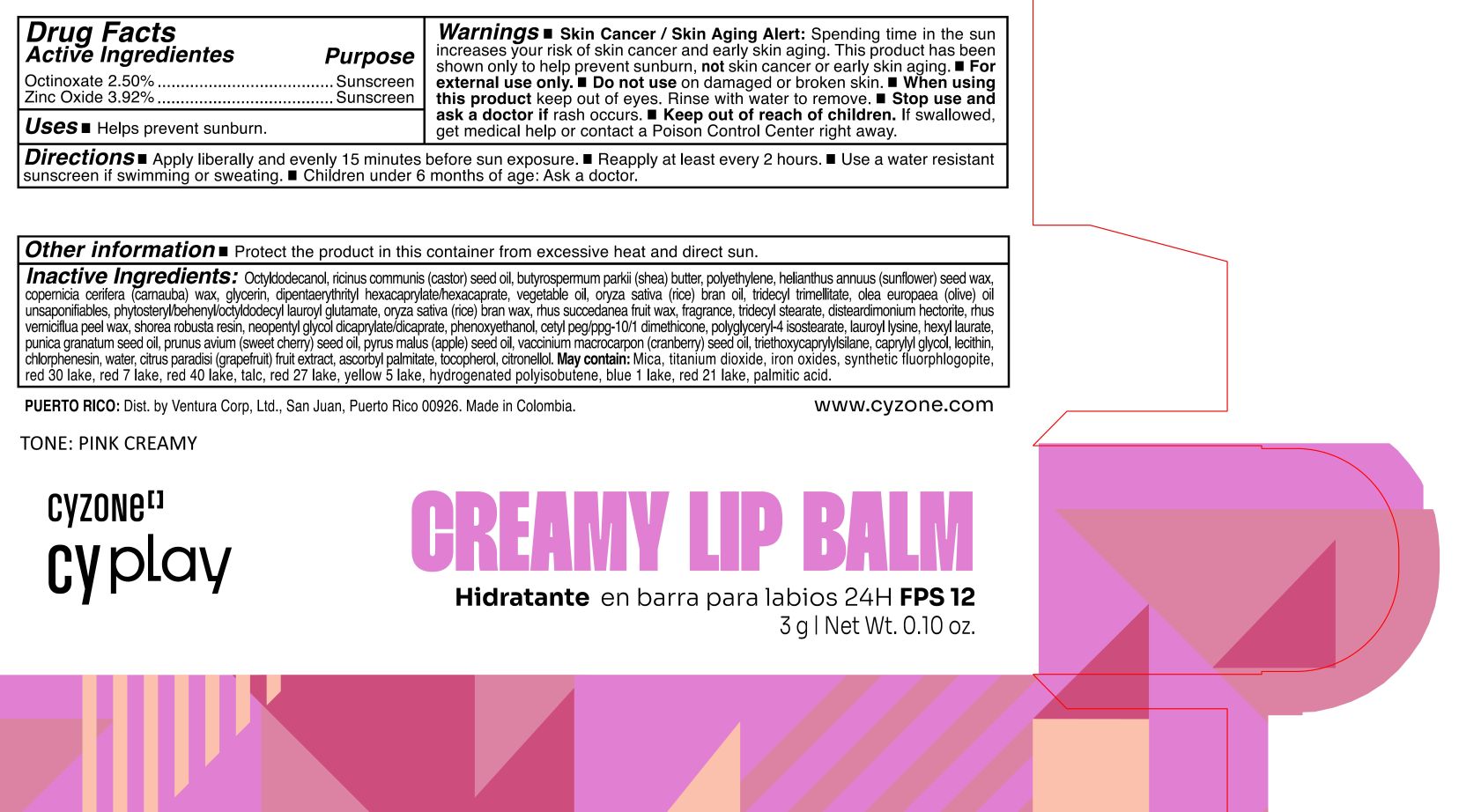 DRUG LABEL: CYZONE CY PLAY CREAMY LIP BALM HIDRATANTE EN BARRA PARA LABIOS 24H FPS 12 CORAL CREAMY
NDC: 14141-309 | Form: STICK
Manufacturer: BEL STAR S A
Category: otc | Type: HUMAN OTC DRUG LABEL
Date: 20250821

ACTIVE INGREDIENTS: ZINC OXIDE 39.2 mg/1 g; OCTINOXATE 25 mg/1 g
INACTIVE INGREDIENTS: SHOREA ROBUSTA RESIN; LAUROYL LYSINE; TRIETHOXYCAPRYLYLSILANE; D&C RED NO. 30; GRAPEFRUIT; ASCORBYL PALMITATE; TOCOPHEROL; .BETA.-CITRONELLOL, (R)-; MICA; TITANIUM DIOXIDE; CARNAUBA WAX; CORN OIL; D&C RED NO. 7; FERROSOFERRIC OXIDE; D&C RED NO. 27; FERRIC OXIDE RED; FD&C BLUE NO. 1 ALUMINUM LAKE; SWEET CHERRY SEED OIL; NEOPENTYL GLYCOL DICAPRYLATE/DICAPRATE; CAPRYLYL GLYCOL; CHLORPHENESIN; WATER; LECITHIN, SUNFLOWER; HIGH DENSITY POLYETHYLENE; GLYCERIN; RICE BRAN OIL; OLEA EUROPAEA (OLIVE) OIL UNSAPONIFIABLES; FERRIC OXIDE YELLOW; PALMITIC ACID; TALC; HELIANTHUS ANNUUS SEED WAX; DISTEARDIMONIUM HECTORITE; CRANBERRY SEED OIL; FD&C RED NO. 40; MAGNESIUM POTASSIUM ALUMINOSILICATE FLUORIDE; RICE BRAN; PHENOXYETHANOL; APPLE SEED OIL; TOXICODENDRON SUCCEDANEUM FRUIT WAX; DIPENTAERYTHRITYL HEXACAPRYLATE/HEXACAPRATE; TRIDECYL TRIMELLITATE; TOXICODENDRON VERNICIFLUUM FRUIT RIND WAX; POLYGLYCERYL-4 ISOSTEARATE; TRIDECYL STEARATE; PUNICA GRANATUM SEED OIL; HYDROGENATED POLYBUTENE (1300 MW); OCTYLDODECANOL; CASTOR OIL; SHEA BUTTER; CETYL PEG/PPG-10/1 DIMETHICONE (HLB 2); HEXYL LAURATE; FD&C YELLOW NO. 5; D&C RED NO. 21 ALUMINUM LAKE

CYZONE CY PLAY CREAMY LIP BALM HIDRATANTE EN BARRA PARA LABIOS 24H FPS 12

Active Ingredients

Octinoxate 2.50%

Zinc Oxide 3.92%

Purpose

Sunscreen

Uses

- Helps prevent sunburn.

Warnings

- Skin Cancer / Skin Aging Alert: Spending time in the sun increases your risk of skin cancer and early skin aging. This product has been shown only to help prevent sunburn, not skin cancer or early skin aging.
- For external use only.

Do not use

on damaged or broken skin.

When using this product

keep out of eyes. Rinse with water to remove.

Stop use and ask a doctor if

rash occurs.

Keep out of reach of children.

If swallowed, get medical help or contact a Poison Control Center right away.

Directions

- Apply liberally and evenly 15 minutes before sun exposure.
- Reapply at least every 2 hours.
- Use a water resistant sunscreen if swimming or sweating.
- Children under 6 months of age: Ask a doctor.

Other information

- Protect the product in this container from excessive heat and direct sun.

Inactive Ingredients

Octyldodecanol, ricinus communis (castor) seed oil, butyrospermum parkii (shea) butter, polyethylene, helianthus annuus (sunflower) seed wax, copernicia cerifera (carnauba) wax, glycerin, dipentaerythrityl hexacaprylate/hexacaprate, vegetable oil, oryza sativa (rice) bran oil, tridecyl trimellitate, olea europaea (olive) oil unsaponifiables, phytosteryl/behenyl/octyldodecyl lauroyl glutamate, oryza sativa (rice) bran wax, rhus succedanea fruit wax, fragrance, tridecyl stearate, disteardimonium hectorite, rhus verniciflua peel wax, shorea robusta resin, neopentyl glycol dicaprylate/dicaprate, phenoxyethanol, cetyl peg/ppg-10/1 dimethicone, polyglyceryl-4 isostearate, lauroyl lysine, hexyl laurate, punica granatum seed oil, prunus avium (sweet cherry) seed oil, pyrus malus (apple) seed oil, vaccinium macrocarpon (cranberry) seed oil, triethoxycaprylylsilane, caprylyl glycol, lecithin, chlorphenesin, water, citrus paradisi (grapefruit) fruit extract, ascorbyl palmitate, tocopherol, citronellol.

May contain:

Mica, titanium dioxide, iron oxides, synthetic fluorphlogopite, red 30 lake, red 7 lake, red 40 lake, talc, red 27 lake, yellow 5 lake, hydrogenated polyisobutene, blue 1 lake, red 21 lake, palmitic acid.

Company Information

PUERTO RICO: Dist. by Ventura Corp, Ltd., San Juan, Puerto Rico 00926. Made in Colombia.

www.cyzone.com